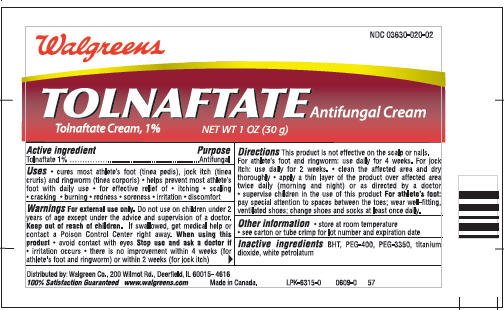 DRUG LABEL: Tolnaftate
NDC: 61360-2020 | Form: CREAM
Manufacturer: Taro Pharmaceuticals, Inc.
Category: otc | Type: HUMAN OTC DRUG LABEL
Date: 20091204

ACTIVE INGREDIENTS: Tolnaftate 1 g/100 g
INACTIVE INGREDIENTS: BUTYLATED HYDROXYTOLUENE; POLYETHYLENE GLYCOL 400; POLYETHYLENE GLYCOL 3350; titanium dioxide; petrolatum

TOLNAFTATE Antifungal Cream

Active ingredient

Tolnaftate 1%

Purpose

Antifungal

Uses

- cures most athlete's foot (tinea pedis), jock itch (tinea cruris) and ringworm (tinea corporis)
- helps prevent most athlete's foot with daily use
- for effective relief of
  - itching
  - scaling
  - cracking
  - burning
  - redness
  - soreness
  - irritation
  - discomfort

Warnings

For external use only.

Do not use on children under 2 years of age except under the advice and supervision of a doctor.

Keep out of reach of children. If swallowed, get medical help or contact a Poison Control Center right away.

When using this product

- avoid contact with eyes

Stop use and ask a doctor if

- irritation occurs
- there is no improvement within 4 weeks (for athlete's foot and ringworm) or within 2 weeks (for jock itch)

Directions

This product is not effective on the scalp or nails.

For athlete's foot and ringworm

use daily for 4 weeks.

For jock itch

use daily for 2 weeks

- clean the affected area and dry thoroughly
- apply a thin layer of the product over affected area twice daily (morning and night) or as directed by a doctor
- supervise children in the use of this product

For athlete's foot

pay special attention to spaces between the toes; wear well-fitting, ventilated shoes, change shoes and socks at least once daily.

Other information

- store at room temperature
- see carton or tube crimp for lot number and expiration date

Inactive ingredients

BHT, PEG-400, PEG-3350, titanium dioxide, white petrolatum

Distributed by: Walgreen Co., 200 Wilmot Rd., Deerfield, IL 60015-4616

100% Satisfaction Guaranteed
www.walgreens.com

Made in Canada.

PRINCIPAL DISPLAY PANEL - 30 g Label

Walgreens

NDC 03630-020-02

TOLNAFTATE Antifungal Cream

Tolnaftate Cream, 1%
NET WT 1 OZ (30 g)